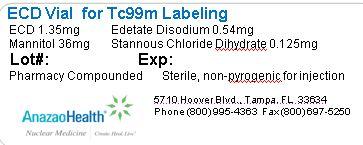 DRUG LABEL: Bicisate
NDC: 51808-217 | Form: INJECTION, POWDER, LYOPHILIZED, FOR SOLUTION
Manufacturer: AnazaoHealth Corporation
Category: prescription | Type: HUMAN PRESCRIPTION DRUG LABEL
Date: 20120523

ACTIVE INGREDIENTS: BICISATE 1.35 mg/1 1
INACTIVE INGREDIENTS: EDETATE DISODIUM 0.54 mg/1 1; MANNITOL 36 mg/1 1; STANNOUS CHLORIDE 0.125 mg/1 1

Bicisate (ECD)
(for the preparation of Tc99m Bicisate injection)

Dear Medical Professional,

Per your order, we have compounded ECD as a sterile freeze-dried preparation. The characteristics of this preparation are:

DESCRIPTION

AnazaoHealth supplies ECD as a compounded kit for preparing Tc99m ECD. Each Reaction vial contains 1.35 mg of ECD, 0.54 edetate disodium, 36mg mannitol and 0.125 mg stannous chloride dehydrate. The vial is back filled with inert gas and may contain a partial vacuum.

Each ECD buffer vial contains a total volume of 1 mL that includes 6.15 mg sodium phosphate dibasic and 0.69 mg sodium phosphate monobasic

CLINICAL PHARMACOLOGY

Tc99m Bicisate forms a stable, lipophilic complex that crosses intact cell membranes and blood brain barrier by passive diffusion. The amount of tc99m bicisate is stable in the brain until about 6 hours

INDICATIONS AND USAGE

Tc99m bicisate is indicated as an adjunct to conventional CT or MRI imaging in the localization of stroke in patients in whom stroke has already been diagnosed

HALF-LIFE

The physical half-life for Technetium is 6.02 hours

CONTRAINDICATIONS

There are no known contraindications for this preparation.

DOSAGE AND ADMINISTRATION

The recommended dose for a 70 kg patient is 10-30 mCi

PREPARATION

For best results, use tc99m from a generator eluted within 24 hours. The eluate should be used within 2 hours of elution.

Reconstitution Instructions:

1. Snap off the plastic lid and place in appropriate lead shielding. Wipe the septum with 70% isopropyl alcohol and allow it to dry.
2. Using a 10 mL syringe, draw up 100 mCi of tc99m (in approximately 2 mL) and inject into the ECD Buffer, being sure to withdraw an equal amount of gas from the vial to neutralize pressure.
3. With a sterile syringe, inject 3 mL of 0.9% sodium chloride into the reaction vial to dissolve the contents. Remove an equal volume of air to maintain pressure within the vial. Shake the contents of the vial for a few seconds.
4. With another sterile syringe, immediately (within 30 seconds) withdraw 1 mL out of the reaction vial and inject it into the buffer vial. Discard the reaction vial
5. Swirl the contents of the buffer vial for a few seconds and allow this mixture to stand for 30 minutes at room temperature.
6. Examine the vial contents for particulates and discoloration prior to patient administration. It should be clear of any particulates.

It is recommended that the kit be stored refrigerated until use; at such time the product should be aseptically withdrawn

Storage and Handling

This kit should be stored in the refrigerator prior to reconstitution and the reaction vial protected from light.

PACKAGE LABEL.PRINCIPAL DISPLAY PANEL

Figure 1